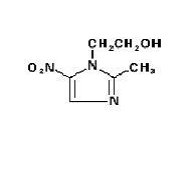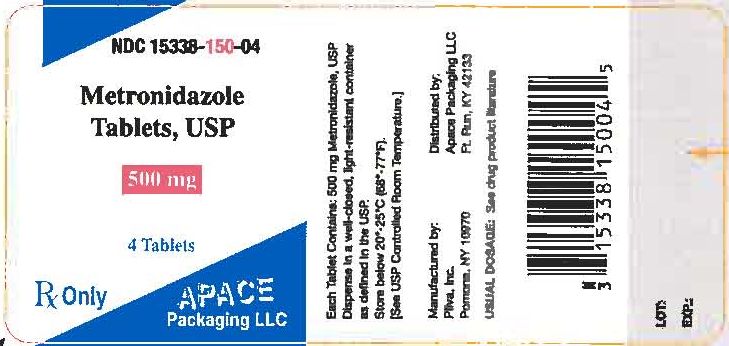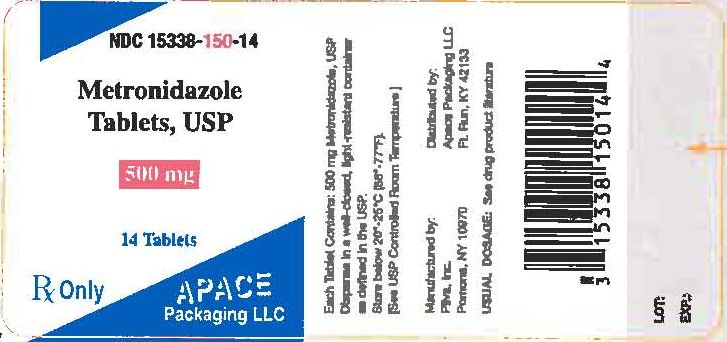 DRUG LABEL: Metronidazole
NDC: 15338-150 | Form: TABLET
Manufacturer: Apace Packaging
Category: prescription | Type: HUMAN PRESCRIPTION DRUG LABEL
Date: 20091229

ACTIVE INGREDIENTS: METRONIDAZOLE 500 mg/1 1
INACTIVE INGREDIENTS: CELLULOSE, MICROCRYSTALLINE; CROSPOVIDONE; SILICON DIOXIDE

METRONIDAZOLE TABLETS, USP

WARNING: Metronidazole has been shown to be carcinogenic in mice and rats. (See PRECAUTIONS.) Unnecessary use of this drug should be avoided. Its use should be reserved for the conditions described in the INDICATIONS AND USAGE section below.

DESCRIPTION:

Metronidazole is an oral synthetic antiprotozoal and antibacterial agent, 1 (β-hydroxyethyl)-2-methyl-5-nitroimidazole, which has the following structural formula:

C6H9N3O3 M.W. 171.16

Each tablet for oral administration contains 250 mg or 500 mg metronidazole. Inactive ingredients include microcrystalline cellulose, crospovidone, colloidal silicon dioxide and hydrogenated vegetable oil.

CLINICAL PHARMACOLOGY:

Disposition of metronidazole in the body is similar for both oral and intravenous dosage forms, with an average elimination half-life in healthy humans of eight hours.

The major route of elimination of metronidazole and its metabolites is via the urine (60-80% of the dose), with fecal excretion accounting for 6-15% of the dose. The metabolites that appear in the urine result primarily from side-chain oxidation [1-(β-hydroxyethyl)-2-hydroxymethyl-5-nitroimidazole and 2-methyl-5-nitroimidazole-1-yl-acetic acid] and glucuronide conjugation, with unchanged metronidazole accounting for approximately 20% of the total. Renal clearance of metronidazole is approximately 10 mL/min/1.73m^2.

Metronidazole is the major component appearing in the plasma, with lesser quantities of the 2-hydroxymethyl metabolite also being present. Less than 20% of the circulating metronidazole is bound to plasma proteins. Both the parent compound and the metabolite possess in vitro bactericidal activity against most strains of anaerobic bacteria and in vitro trichomonacidal activity.

Metronidazole appears in cerebrospinal fluid, saliva, and human milk in concentrations similar to those found in plasma. Bactericidal concentrations of metronidazole have also been detected in pus from hepatic abscesses.

Following oral administration, metronidazole is well absorbed, with peak plasma concentrations occurring between one and two hours after administration. Plasma concentrations of metronidazole are proportional to the administered dose. Oral administration of 250 mg, 500 mg, or 2,000 mg produced peak plasma concentrations of 6 mcg/mL, 12 mcg/mL, and 40 mcg/mL, respectively. Studies reveal no significant bioavailability differences between males and females; however, because of weight differences, the resulting plasma levels in males are generally lower.

Decreased renal function does not alter the single-dose pharmacokinetics of metronidazole. However, plasma clearance of metronidazole is decreased in patients with decreased liver function.

Microbiology: Trichomonas vaginalis, Entamoeba histolytica: Metronidazole possesses direct trichomonacidal and amebacidal activity against T. vaginalis and E. histolytica. The in vitro minimal inhibitory concentration (MIC) for most strains of these organisms is 1 mcg/mL or less.

Anaerobic Bacteria: Metronidazole is active in vitro against most obligate anaerobes but does not appear to possess any clinically relevant activity against facultative anaerobes or obligate aerobes. Against susceptible organisms, metronidazole is generally bactericidal at concentrations equal to or slightly higher than the minimal inhibitory concentrations. Metronidazole has been shown to have in vitro and clinical activity against the following organisms:

Anaerobic gram-negative bacilli, including:

Bacteroides species including the Bacteroides fragilis group (B. fragilis, B. distasonis, B. ovatus, B. thetaiotaomicron, B. vulgatus).

Fusobacterium species.

Anaerobic gram-positive bacilli, including:

Clostridium species and susceptible strains of Eubacterium.

Anaerobic gram-positive cocci, including:

Peptococcus niger, Peptostreptococcus species.

Susceptibility Tests: Bacteriologic studies should be performed to determine the causative organisms and their susceptibility to metronidazole; however, the rapid, routine susceptibility testing of individual isolates of anaerobic bacteria is not always practical, and therapy may be started while awaiting these results.

Quantitative methods give the most precise estimates of susceptibility to antibacterial drugs. A standardized agar dilution method and a broth microdilution method are recommended^1.

Control strains are recommended for standardized susceptibility testing. Each time the test is performed, one or more of the following strains should be included: Clostridium perfringens ATCC 13124. Bacteroides fragilis ATCC 25285, and Bacteroides thetaiotaomicron ATCC 29741. The mode metronidazole MICs for those three strains are reported to be 0.25, 0.25, and 0.5 mcg/mL, respectively.

A clinical laboratory is considered under acceptable control if the results of the control strains are within one doubling dilution of the mode MICs reported for metronidazole.

A bacterial isolate may be considered susceptible if the MIC value for metronidazole is not more than 16 mcg/mL. An organism is considered resistant if the MIC is greater than 16 mcg/mL. A report of “resistant” from the laboratory indicates that the infecting organism is not likely to respond to therapy.

INDICATIONS AND USAGE:

Symptomatic Trichomoniasis: Metronidazole is indicated for the treatment of symptomatic trichomoniasis in females and males when the presence of the trichomonad has been confirmed by appropriate laboratory procedures (wet smears and/or cultures).

Asymptomatic Trichomoniasis: Metronidazole is indicated in the treatment of asymptomatic females when the organism is associated with endocervicitis, cervicitis, or cervical erosion.Since there is evidence that presence of the trichomonad can interfere with accurate assessment of abnormal cytological smears, additional smears should be performed after eradication of the parasite.

Treatment of Asymptomatic Consorts: T. vaginalis infection is a venereal disease. Therefore, asymptomatic sexual partners of treated patients should be treated simultaneously if the organism has been found to be present, in order to prevent reinfection of the partner. The decision as to whether to treat an asymptomatic male partner who has a negative culture or one for whom no culture has been attempted is an individual one. In making this decision, it should be noted that there is evidence that a woman may become reinfected if her consort is not treated. Also, since there can be considerable difficulty in isolating the organism from the asymptomatic male carrier, negative smears and cultures cannot be relied upon in this regard. In any event, the consort should be treated with metronidazole in cases of reinfection.

Amebiasis: Metronidazole is indicated in the treatment of acute intestinal amebiasis (amebic dysentery) and amebic liver abscess. In amebic liver abscess, metronidazole therapy does not obviate the need for aspiration or drainage of pus.

Anaerobic Bacterial Infections: Metronidazole is indicated in the treatment of serious infections caused by susceptible anaerobic bacteria. Indicated surgical procedures should be performed in conjunction with metronidazole therapy. In a mixed aerobic and anaerobic infection, antimicrobials appropriate for the treatment of the aerobic infection should be used in addition to metronidazole.

In the treatment of most serious anaerobic infections, the intravenous form of metronidazole is usually administered initially. This may be followed by oral therapy with metronidazole at the discretion of the physician.

Intra-Abdominal Infections, including peritonitis, intra-abdominal abscess, and liver abscess, caused by Bacteroides species, including the B. fragilis group, (B. fragilis, B. distasonis, B. ovatus, B. thetaiotaomicron, B. vulgatus), Clostridium species, Eubacterium species, Peptococcus niger, and Peptostreptococcus species.

Skin and Skin Structure Infections caused by Bacteroides species including the B. fragilis group, Clostridium species, Peptococcus niger, Peptostreptococcus species, and Fusobacterium species.

Gynecologic Infections, including endometritis, endomyometritis, tubo-ovarian abscess, and postsurgical vaginal cuff infection, caused by Bacteroides species including the B. fragilis group, Clostridium species, Peptococcus niger and Peptostreptococcus species.

Bacterial Septicemia caused by Bacteroides species including the B. fragilis group and Clostridium species.

Bone and Joint Infections, as adjunctive therapy, caused by Bacteroides species, including the B. fragilis group.

Central Nervous System (CNS) Infection, including meningitis and brain abscess, caused by Bacteroides species, including the B. fragilis group.

Lower Respiratory Tract Infections, including pneumonia, empyema, and lung abscess, caused by Bacteroides species including the B. fragilis group.

Endocarditis caused by Bacteroides species including the B. fragilis group.

CONTRAINDICATIONS:

Metronidazole is contraindicated in patients with a prior history of hypersensitivity to metronidazole or other nitroimidazole derivatives.

WARNINGS:

Convulsive Seizures and Peripheral Neuropathy: Convulsive seizures and peripheral neuropathy, the latter characterized mainly by numbness or paresthesia of an extremity, have been reported in patients treated with metronidazole. The appearance of abnormal neurological signs demands the prompt discontinuation of metronidazole therapy. Metronidazole should be administered with caution to patients with central nervous system diseases.

PRECAUTIONS:

General:

Patients with severe hepatic disease metabolize metronidazole slowly, with resultant accumulation of metronidazole and its metabolites in the plasma. Accordingly, for such patients, doses below those usually recommended should be administered cautiously.

Known or previously unrecognized candidiasis may present more prominent symptoms during therapy with metronidazole and requires treatment with a candicidal agent.

Information for Patients:

Alcoholic beverages should be avoided while taking metronidazole and for at least one day afterward. See Drug Interactions.

Laboratory Tests:

Metronidazole is a nitroimidazole and should be used with caution in patients with evidence of or history of blood dyscrasia. A mild leukopenia has been observed during its administration; however, no persistent hematologic abnormalities attributable to metronidazole have been observed in clinical studies. Total and differential leukocyte counts are recommended before and after therapy for trichomoniasis and amebiasis, especially if a second course of therapy is necessary, and before and after therapy for anaerobic infections.

Drug Interactions:

Metronidazole has been reported to potentiate the anticoagulant effect of warfarin and other oral coumarin anticoagulants, resulting in a prolongation of prothrombin time. This possible drug interaction should be considered when metronidazole is prescribed for patients on this type of anticoagulant therapy.

The simultaneous administration of drugs that induce microsomal liver enzymes, such as phenytoin or phenobarbital, may accelerate the elimination of metronidazole, resulting in reduced plasma levels; impaired clearance of phenytoin has also been reported.

The simultaneous administration of drugs that decrease microsomal liver enzyme activity, such as cimetidine, may prolong the half-life and decrease plasma clearance of metronidazole. In patients stabilized on relatively high doses of lithium, short-term metronidazole therapy has been associated with elevation of serum lithium and, in a few cases, signs of lithium toxicity. Serum lithium and serum creatinine levels should be obtained several days after beginning metronidazole to detect any increase that may precede clinical symptoms of lithium intoxication.

Alcoholic beverages should not be consumed during metronidazole therapy and for at least one day afterward because abdominal cramps, nausea, vomiting, headaches, and flushing may occur.

Psychotic reactions have been reported in alcoholic patients who are using metronidazole and disulfiram concurrently. Metronidazole should not be given to patients who have taken disulfiram within the last two weeks.

Drug/Laboratory Test Interactions:

Metronidazole may interfere with certain types of determinations of serum chemistry values, such as aspartate aminotransferase (AST, SGOT), alanine aminotransferase (ALT, SGPT), lactate dehydrogenase (LDH), triglycerides, and hexokinase glucose. Values of zero may be observed. All of the assays in which interference has been reported involve enzymatic coupling of the assay to oxidation-reduction of nicotinamide adenine dinucleotide (NAD+ ⇌NADH). Interference is due to the similarity in absorbance peaks of NADH (340 nm) and metronidazole (322 nm) at pH 7.

Carcinogenesis, Mutagenesis, Impairment of Fertility:

Metronidazole has shown evidence of carcinogenic activity in a number of studies involving chronic, oral administration in mice and rats.

Prominent among the effects in the mouse was the promotion of pulmonary tumorigenesis. This has been observed in all six reported studies in that species, including one study in which the animals were dosed on an intermittent schedule (administration during every fourth week only). At very high dose levels (approximately 500 mg/kg/day which is approximately 33 times the most frequently recommended human dose for a 50 kg adult based on mg/kg body weight) there was a statistically significant increase in the incidence of malignant liver tumors in males. Also, the published results of one of the mouse studies indicate an increase in the incidence of malignant lymphomas as well as pulmonary neoplasms associated with lifetime feeding of the drug. All these effects are statistically significant.

Several long-term, oral-dosing studies in the rat have been completed. There were statistically significant increases in the incidence of various neoplasms, particularly in mammary and hepatic tumors, among female rats administered metronidazole over those noted in the concurrent female control groups.

Two lifetime tumorigenicity studies in hamsters have been performed and reported to be negative.

Although metronidazole has shown mutogenic activity in a number of in vivo assay systems, studies in mammals (in vivo) have failed to demonstrate a potential for genetic damage.

Fertility studies have been performed in mice at doses up to six times the maximum recommended human dose based on mg per sq. m. and have revealed no evidence of impaired fertility.

Pregnancy:

Teratogenic Effects - Pregnancy Category B.

Metronidazole crosses the placental barrier and enters the fetal circulation rapidly. Reproduction studies have been performed in rats at doses up to five times the human dose and have revealed no evidence of impaired fertility or harm to the fetus due to metronidazole. No fetotoxicity was observed when metronidazole was administered orally to pregnant mice at 20 mg/kg/day approximately one and a half times the most frequently recommended human dose (750 mg/day) based on mg/kg body weight; however, in a single small study where the drug was administered intraperitoneally, some intrauterine deaths were observed.

The relationship of these findings to the drug is unknown. There are, however, no adequate and well-controlled studies in pregnant women. Because animal reproduction studies are not always predictive of human response, and because metronidazole is a carcinogen in rodents, this drug should be used during pregnancy only if clearly needed.

Use of metronidazole for trichomoniasis during pregnancy should be restricted to those in whom alternative treatment has been inadequate. Use of metronidazole for trichomoniasis in the first trimester of pregnancy should be carefully evaluated because metronidazole crosses the placental barrier and its effects on the human fetal organogenesis are not known (see above).

Nursing Mothers:

Because of the potential for tumorigenicity, shown for metronidazole in mouse and rat studies, a decision should be made whether to discontinue nursing or to discontinue the drug, taking into account the importance of the drug to the mother. Metronidazole is secreted in human milk in concentrations similar to those found in plasma.

Geriatric Use:

Decreased renal function does not alter the single-dose pharmacokinetics of metronidazole. However, plasma clearance of metronidazole is decreased in patients with decreased liver function. Therefore, in elderly patients, monitoring of serum levels may be necessary to adjust the metronidazole dosage accordingly.

Pediatric Use:

Safety and effectiveness in pediatric patients have not been established, except for the treatment of amebiasis.

ADVERSE REACTIONS:

Two serious adverse reactions reported in patients treated with metronidazole have been convulsive seizures and peripheral neuropathy, the latter characterized mainly by numbness or paresthesia of an extremity. Since persistent peripheral neuropathy has been reported in some patients receiving prolonged administration of metronidazole, patients should be specifically warned about these reactions and should be told to stop the drug and report immediately to their physicians if any neurologic symptoms occur.

The most common adverse reactions reported have been referable to the gastrointestinal tract, particularly nausea, reported by about 12% of patients, sometimes accompanied by headache, anorexia, and occasionally vomiting; diarrhea; epigastric distress; and abdominal cramping. Constipation has also been reported.

The following reactions have also been reported during treatment with metronidazole:

Mouth: A sharp, unpleasant metallic taste is not unusual. Furry tongue, glossitis, and stomatitis have occurred; these may be associated with a sudden overgrowth of Candida which may occur during therapy.

Hematopoietic: Reversible neutropenia (leukopenia); rarely reversible thrombocytopenia.

Cardiovascular: Flattening of the T-wave may be seen in electrocardiographic tracings.

Central Nervous System: Convulsive seizures, peripheral neuropathy, dizziness, vertigo, incoordination, ataxia, confusion, irritability, depression, weakness, and insomnia.

Hypersensitivity: Urticaria, erythematosus rash, flushing, nasal congestion, dryness of the mouth (or vagina or vulva) and fever.

Renal: Dysuria, cystitis, polyuria, incontinence, and a sense of pelvic pressure. Instances of darkened urine have been reported by approximately one patient in 100,000. Although the pigment which is probably responsible for this phenomenon has not been positively identified, it is almost certainly a metabolite of metronidazole and seems to have no clinical significance.

Other: Proliferation of Candida in the vagina, dyspareunia, decrease of libido, proctitis, and fleeting joint pains sometimes resembling ‘serum sickness’. If patients receiving metronidazole drink alcoholic beverages, they may experience abdominal distress, nausea, vomiting, flushing, or headache. A modification of the taste of alcoholic beverages has also been reported. Rare cases of pancreatitis, which generally abated on withdrawal of the drug, have been reported.

Crohn’s disease patients are known to have an increased incidence of gastrointestinal and certain extraintestinal cancers. There have been some reports in the medical literature of breast and colon cancer in Crohn’s disease patients who have been treated with metronidazole at high doses for extended periods of time. A cause and effect relationship has not been established. Crohn’s disease is not an approved indication for metronidazole.

OVERDOSAGE:

Single oral doses of metronidazole, up to 15 g, have been reported in suicide attempts and accidental overdoses. Symptoms reported include nausea, vomiting, and ataxia.

Oral metronidazole has been studied as a radiation sensitizer in the treatment of malignant tumors. Neurotoxic effects, including seizures and peripheral neuropathy, have been reported after 5 to 7 days of doses of 6 to 10.4 g every other day.

Treatment: There is no specific antidote for metronidazole overdose; therefore, management of the patient should consist of symptomatic and supportive therapy.

DOSAGE AND ADMINISTRATION:

In elderly patients, the pharmacokinetics of metronidazole may be altered, and, therefore, monitoring of serum levels may be necessary to adjust the metronidazole dosage accordingly.

Trichomoniasis:

In the Female:

One day treatment: Two grams of metronidazole given either as a single dose or in two divided doses of one gram each given in the same day.

Seven-day course of treatment: 250 mg three times daily for seven consecutive days. There is some indication from controlled comparative studies that cure rates as determined by vaginal smears, signs and symptoms, may be higher after a seven-day course of treatment than after a one day treatment regimen.

The dosage regimen should be individualized. Single-dose treatment can assure compliance, especially if administered under supervision, in those patients who cannot be relied on to continue the seven-day regimen. A seven-day course of treatment may minimize reinfection by protecting the patient long enough for the sexual contacts to obtain appropriate treatment. Further, some patients may tolerate one treatment regimen better than the other.

In pregnant patients in whom alternative treatment has been inadequate, the one-day course of therapy should not be used, as it results in higher serum levels which can reach the fetal circulation (see PRECAUTIONS: Pregnancy).

When repeat courses of the drug are required, it is recommended that an interval of four to six weeks elapse between courses and that the presence of the trichomonad be reconfirmed by appropriate laboratory measures. Total and differential leukocyte counts should be made before and after re-treatment.

In the Male:

Treatment should be individualized as for the female.

Amebiasis:

Adults:

For Acute Intestinal Amebiasis (Acute Amebic Dysentery): 750 mg orally three times daily for 5 to 10 days.

For Amebic Liver Abscess: 500 mg or 750 mg orally three times daily for 5 to 10 days.

Children:

35 to 50 mg/kg/24 hours, divided into three doses, orally for 10 days.

Anaerobic Bacterial Infections: In the treatment of most serious anaerobic infections, the intravenous form of metronidazole is usually administered initially.

The usual adult oral dosage is 7.5 mg/kg every six hours (approx. 500 mg for a 70 kg adult). A maximum of 4 g should not be exceeded during a 24 hour period.

The usual duration of therapy is 7 to 10 days; however, infections of the bone and joint, lower respiratory tract, and endocardium may require longer treatment.

Patients with severe hepatic disease metabolize metronidazole slowly, with resultant accumulation of metronidazole and its metabolites in the plasma. Accordingly, for such patients, doses below those usually recommended should be administered cautiously. Close monitoring of plasma metronidazole levels^2 and toxicity is recommended.

The dose of metronidazole should not be specifically reduced in anuric patients since accumulated metabolites may be rapidly removed by dialysis.

HOW SUPPLIED:

Metronidazole Tablets, USP:

250 mg - White, round, convex, unscored tablets in bottles of 100, 250, 500 and 1000.
Debossed: PLIVA 333

500 mg - White, oblong, convex, unscored tablets in bottles of 100, 500 and 1000.
Debossed: PLIVA 334

Dispense in a well-closed, light-resistant container as defined in the USP. Store at 20°-25°C (68°-77°F) [See USP Controlled Room Temperature]. Protect from light.

REFERENCES

1. Proposed standard: PSM-11-Proposed Reference Dilution Procedure for Antimicrobic Susceptibility Testing of Anaerobic Bacteria, National Committee for Clinical Laboratory Standards, and Sutter, et al: Collaborative Evaluation of a Proposed Reference Dilution Method of Susceptibility Testing of Anaerobic Bacteria, Antimicrob. Agents Chemother. 16:495-502 (Oct.) 1979; and Tally et al: In Vitro Activity of Thienamycin, Antimicrob Agents Chemother. 14:436-438 (Sept.) 1978.

2. Ralph, E.D., and Kirby, WM. M.: Bioassay of Metronidazole With Either Anaerobic or Aerobic Incubation, J. Infect Dis 132:587-591 (Nov.) 1975; or Gulaid, et al.: Determination of Metronidazole and Its Major Metabolites in Biological Fluids by High Pressure Liquid Chromatography, Br. J. Clin. Pharmacol 6:430-432, 1978.

Manufactured by: PLIVA®, Inc., Pomona, NY 10970

Packaged by:
APACE Packaging, LLC
Fountain Run, KY 42133

PRINCIPAL DISPLAY PANEL

NDC 15338-150-04

Metronidazole Tablets, USP

500 mg

4 Tablets

Rx Only

Each Tablet Contains: 500 mg Metronidazole, USP
Dispense in a well-closed, light-resistant container as defined in the USP.
Store at 20°-25°C (68°-77°F).
[See USP Controlled Room Temperature].

USUAL DOSAGE: See drug product literature

PRINCIPAL DISPLAY PANEL

NDC 15338-150-14

Metronidazole Tablets, USP

500 mg

14 Tablets

Rx Only

Each Tablet Contains: 500 mg Metronidazole, USP
Dispense in a well-closed, light-resistant container as defined in the USP.
Store at 20°-25°C (68°-77°F).
[See USP Controlled Room Temperature].

USUAL DOSAGE: See drug product literature